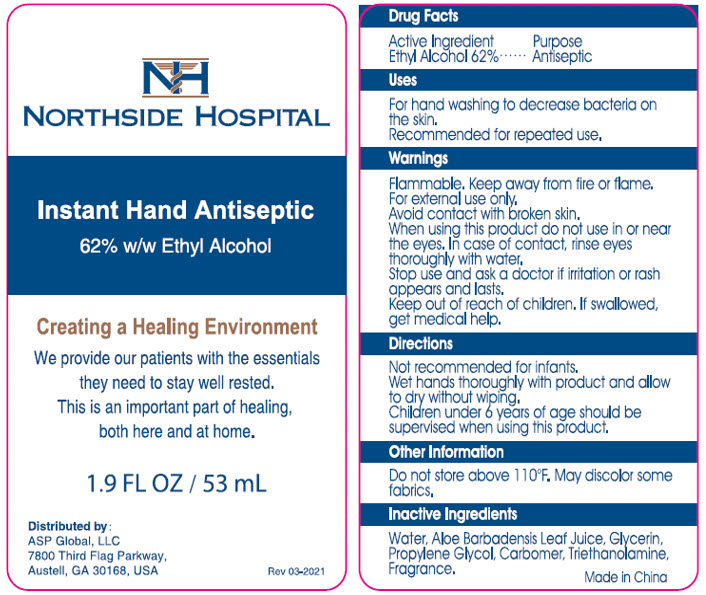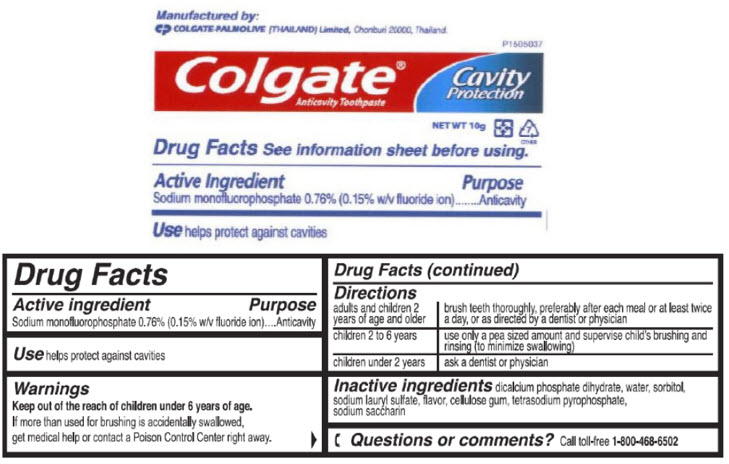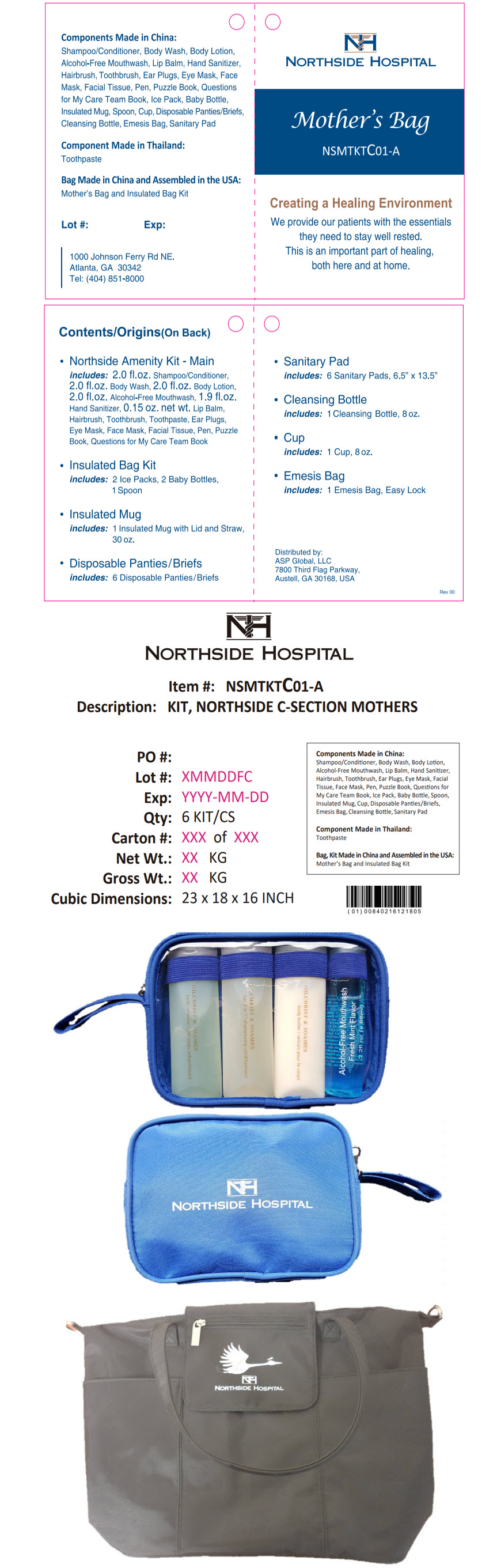 DRUG LABEL: Northside Hospital C-Section Mothers
NDC: 59448-210 | Form: KIT | Route: TOPICAL
Manufacturer: ASP Global, LLc
Category: otc | Type: HUMAN OTC DRUG LABEL
Date: 20241217

ACTIVE INGREDIENTS: ALCOHOL 62 mL/100 mL; SODIUM MONOFLUOROPHOSPHATE 7.6 mg/1 g
INACTIVE INGREDIENTS: Water; Aloe Vera Leaf; Glycerin; Propylene Glycol; CARBOMER INTERPOLYMER TYPE A (ALLYL SUCROSE CROSSLINKED); Trolamine; DIBASIC CALCIUM PHOSPHATE DIHYDRATE; Water; Sorbitol; Sodium Lauryl Sulfate; SODIUM PYROPHOSPHATE; SACCHARIN SODIUM

Northside Hospital C-Section Mother's Kit

Instant Hand Antiseptic

Drug Facts

Active Ingredient

Ethyl Alcohol 62%

Purpose

Antiseptic

Uses

For hand washing to decrease bacteria on the skin.

Recommended for repeated use.

Warnings

Flammable. Keep away from fire or flame.

For external use only.

Avoid contact with broken skin.

When using this product do not use in or near the eyes. In case of contact, rinse eyes thoroughly with water.

Stop use and ask a doctor if irritation or rash appears and lasts.

Keep out of reach of children. If swallowed, get medical help.

Directions

Not recommended for infants.

Wet hands thoroughly with product and allow to dry without wiping.

Children under 6 years of age should be supervised when using this product.

Other Information

Do not store above 110°F. May discolor some fabrics.

Inactive Ingredients

Water, Aloe Barbadensis Leaf Juice, Glycerin, Propylene Glycol, Carbomer, Triethanolamine, Fragrance.

Distributed by:
ASP Global, LLC
7800 Third Flag Parkway,
Austell, GA 30168, USA

Colgate® Anticavity Toothpaste

Drug Facts

Active ingredient

Sodium monofluorophosphate 0.76% (0.15% w/v fluoride ion)

Purpose

Anticavity

Use

helps protect against cavities

Warnings

KEEP OUT OF REACH OF CHILDREN

Keep out of the reach of children under 6 years of age.

If more than used for brushing is accidentally swallowed, get medical help or contact a Poison Control Center right away.

Directions

adults and children 2 years of age and older | brush teeth thoroughly, preferably after each meal or at least twice a day, or as directed by a dentist or physician
children 2 to 6 years | use only a pea sized amount and supervise child's brushing and rinsing (to minimize swallowing)
children under 2 years | ask a dentist or physician

Inactive ingredients

dicalcium phosphate dihydrate, water, sorbitol, sodium lauryl sulfate, flavor, cellulose gum, tetrasodium pyrophosphate, sodium saccharin

Questions or comments?

Call toll-free 1-800-468-6502

Manufactured by:
COLGATE-PALMOLIVE (THAILAND) Limited, Chonburi 20000, Thailand.

PRINCIPAL DISPLAY PANEL - 53 mL Bottle Label

NORTHSIDE HOSPITAL

Instant Hand Antiseptic
62% w/w Ethyl Alcohol

Creating a Healing Environment

We provide our patients with the essentials
they need to stay well rested.
This is an important part of healing,
both here and at home.

1.9 FL OZ / 53 mL

Distributed by:
ASP Global, LLC
7800 Third Flag Parkway,
Austell, GA 30168, USA

Rev 03-2021

PRINCIPAL DISPLAY PANEL - 10 g Tube Label

P1505037

Colgate®
Anticavity Toothpaste

Cavity
Protection

NET WT 10g
7
OTHER

PRINCIPAL DISPLAY PANEL - Kit Label

Components Made in China:
Shampoo/Conditioner, Body Wash, Body Lotion,
Alcohol-Free Mouthwash, Lip Balm, Hand Sanitizer,
Hairbrush, Toothbrush, Ear Plugs, Eye Mask, Face
Mask, Facial Tissue, Pen, Puzzle Book, Questions
for My Care Team Book, Ice Pack, Baby Bottle,
Insulated Mug, Spoon, Cup, Disposable Panties/Briefs,
Cleansing Bottle, Emesis Bag, Sanitary Pad

Component Made in Thailand:
Toothpaste

Bag Made in China and Assembled in the USA:
Mother's Bag and Insulated Bag Kit

Lot #:
Exp:

1000 Johnson Ferry Rd NE.
Atlanta, GA 30342
Tel: (404) 851-8000

NORTHSIDE HOSPITAL

Mother's Bag

NSMTKTC01-A

Creating a Healing Environment

We provide our patients with the essentials
they need to stay well rested.
This is an important part of healing,
both here and at home.

Contents/Origins(On Back)

- Northside Amenity Kit - Main
  includes: 2.0 fl.oz. Shampoo/Conditioner,
  2.0 fl.oz. Body Wash, 2.0 fl.oz. Body Lotion,
  2.0 fl.oz. Alcohol-Free Mouthwash, 1.9 fl.oz.
  Hand Sanitizer, 0.15 oz. net wt. Lip Balm,
  Hairbrush, Toothbrush, Toothpaste, Ear Plugs,
  Eye Mask, Face Mask, Facial Tissue, Pen, Puzzle
  Book, Questions for My Care Team Book
- Insulated Bag Kit
  includes: 2 Ice Packs, 2 Baby Bottles,
  1 Spoon
- Insulated Mug
  includes: 1 Insulated Mug with Lid and Straw,
  30 oz.
- Disposable Panties/Briefs
  includes: 6 Disposable Panties/Briefs
- Sanitary Pad
  includes: 6 Sanitary Pads, 6.5" x 13.5"
- Cleansing Bottle
  includes: 1 Cleansing Bottle, 8 oz.
- Cup
  includes: 1 Cup, 8 oz.
- Emesis Bag
  includes: 1 Emesis Bag, Easy Lock

Distributed by:
ASP Global, LLC
7800 Third Flag Parkway,
Austell, GA 30168, USA

Rev 00

NORTHSIDE HOSPITAL

Item #: NSMTKTC01-A
Description: KIT, NORTHSIDE C-SECTION MOTHERS

PO #:
Lot #: XMMDDFC
Exp: YYYY-MM-DD
Qty: 6 KIT/CS
Carton #: XXX of XXX
Net Wt.: XX KG
Gross Wt.: XX KG
Cubic Dimensions: 23 x 18 x 16 INCH

Components Made in China:
Shampoo/Conditioner, Body Wash, Body Lotion,
Alcohol-Free Mouthwash, Lip Balm, Hand Sanitizer,
Hairbrush, Toothbrush, Ear Plugs, Eye Mask, Facial
Tissue, Face Mask, Pen, Puzzle Book, Questions for
My Care Team Book, Ice Pack, Baby Bottle, Spoon,
Insulated Mug, Cup, Disposable Panties/Briefs,
Emesis Bag, Cleansing Bottle, Sanitary Pad

Component Made in Thailand:
Toothpaste

Bag, Kit Made in China and Assembled in the USA:
Mother's Bag and Insulated Bag Kit

NORTHSIDE HOSPITAL

NORTHSIDE HOSPITAL